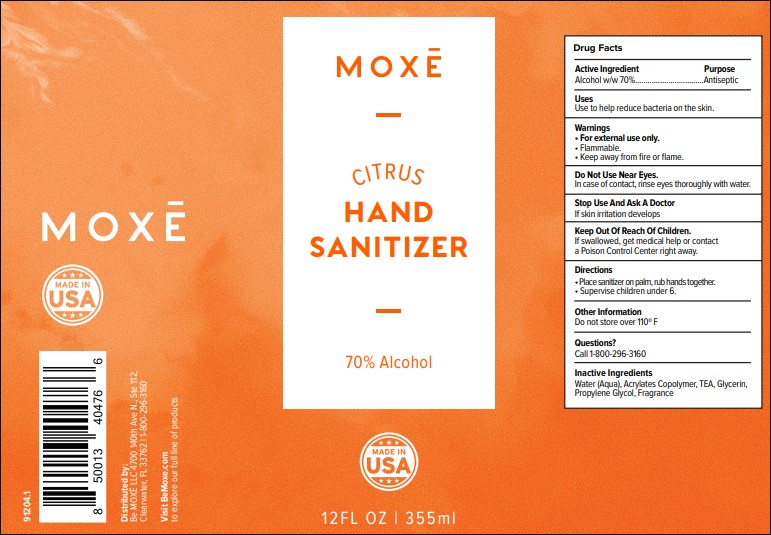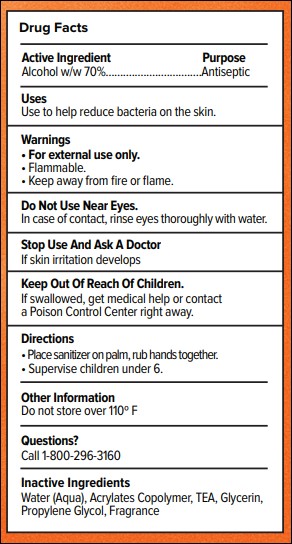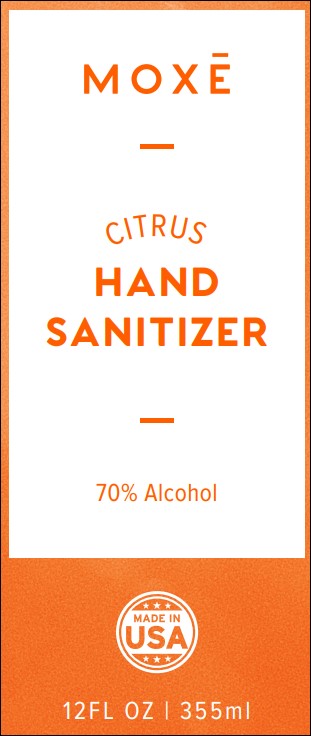 DRUG LABEL: Moxe
NDC: 73333-340 | Form: LOTION
Manufacturer: Nutrix International, LLC.
Category: otc | Type: HUMAN OTC DRUG LABEL
Date: 20200619

ACTIVE INGREDIENTS: ALCOHOL 0.7 g/340 g
INACTIVE INGREDIENTS: CARBOMER 940 0.004 g/340 g; TANGERINE 0.005 g/340 g; GLYCERIN 0.015 g/340 g; WATER 0.2598 g/340 g; TROLAMINE 0.0012 g/340 g

Active Ingredient

Alcohol w/w 70%

Use

Use to help reduce bacteria on the skin

Warnings

• For external use only.

• Flammable.

• Keep away from fire or flame.

Do Not Use Near Eyes. In case of contact, rinse eyes thoroughly with water

Stop Use And Ask A Doctor

If skin irritation develops.

Keep Out Of Reach Of Children.

If swallowed, get medical help or contact a Poison Control Center right away

Directions

• Place sanitizer on palm, rub hands together.

• Supervise children under 6.

Other Information

Do not store over 110º F

Questions?

Call 1-800-296-3160

Inactive Ingredients

Water (Aqua), Acrylates Copolymer, TEA, Glycerin, Propylene Glycol, Fragrance.

Purpose

Antiseptic

Package

Front Label

Drug Fact

Complete Label